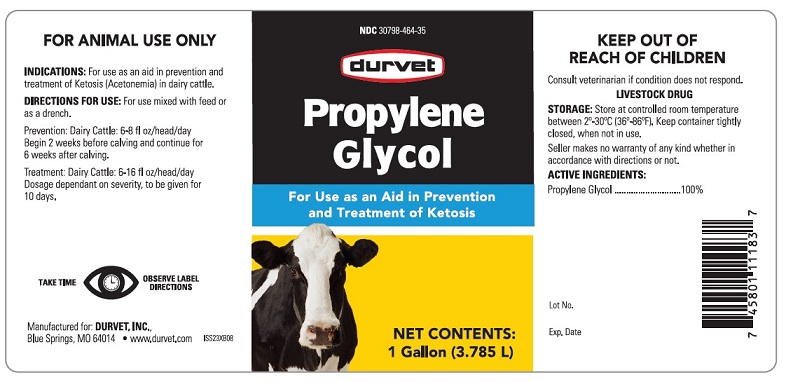 DRUG LABEL: PROPYLENE GLYCOL
NDC: 30798-464 | Form: LIQUID
Manufacturer: Durvet, Inc.
Category: animal | Type: OTC ANIMAL DRUG LABEL
Date: 20250131

ACTIVE INGREDIENTS: PROPYLENE GLYCOL 3.785 L/3.785 L

PROPYLENE GLYCOL, U.S.P.

INDICATIONS AND USAGE

For Use as an Aid in Prevention and Treatment of Ketosis

FOR ANIMAL USE ONLY

KEEP OUT OF REACH OF CHILDREN

Consult veterinarian if condition does not respond.

LIVESTOCK DRUG

INDICATIONS: For use as an aid in prevention and treatment of Ketosis (Acetonemia) in dairy cattle.

DIRECTIONS FOR USE:

For use mixed with feed or as a drench.

Prevent: Dairy Cattle: 6-8 fl oz/.head/day

Begin 2 weeks before calving and continue for 6 weeks after calving.

Treatment: Dairy Cattle: 6-16 fl oz/head/day

Dosage dependent on severity, to be give for 10 days.

TAKE TIME OBSERVE LABEL DIRECTIONS

STORAGE:

Store at controlled room temperature between 2o-30oC (36o-86oF). Keep container tightly closed, when not in use.

Seller makes no warranty of any kind whether in accordance with direction or not.

ACTIVE INGREDIENT:

Propylene Glycol .................. 100%